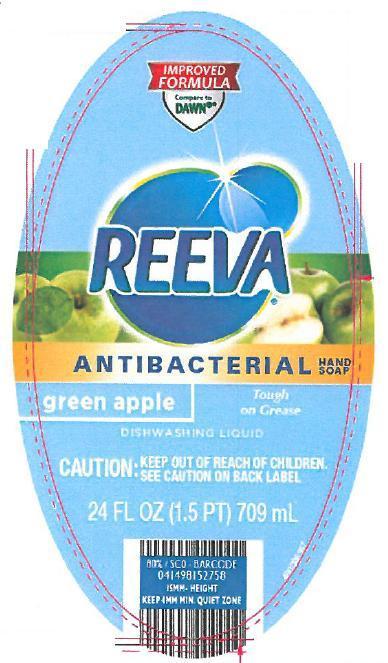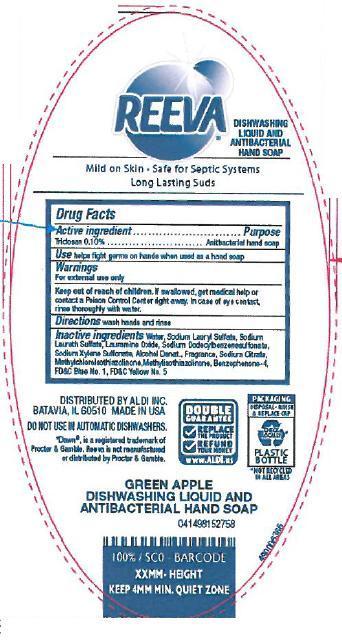 DRUG LABEL: Reeva Antibacterial Green Apple
NDC: 63691-020 | Form: SOAP
Manufacturer: Sun Products Corporation
Category: otc | Type: HUMAN OTC DRUG LABEL
Date: 20151223

ACTIVE INGREDIENTS: TRICLOSAN 0.1 g/100 mL
INACTIVE INGREDIENTS: WATER; SODIUM DODECYLBENZENESULFONATE; SODIUM LAURYL SULFATE; SODIUM LAURETH SULFATE; ALCOHOL; LAURAMINE OXIDE; SODIUM XYLENESULFONATE; SODIUM CITRATE; METHYLCHLOROISOTHIAZOLINONE; METHYLISOTHIAZOLINONE; SULISOBENZONE; FD&C YELLOW NO. 5; FD&C BLUE NO. 1

Active ingredient

Triclosan 0.10%

INDICATIONS AND USAGE

Use helps fight germs on hands when used as a hand soap

WARNINGS

For external use only

Keep out of reach of children. If swallowed, get medical help or contact a Poison Control Center right away. In case of eye contact, rinse thoroughly with water.

DOSAGE AND ADMINISTRATION

Directions wash hands and rinse

PURPOSE

Antibacterial hand soap

INACTIVE INGREDIENT

Inactive ingredients Water, Sodium Lauryl Sulfate, Sodium Laureth Sulfate, Lauramine Oxide, Sodium Dodecylbenzenesulfonate, Sodium Xylene Sulfonate, Alcohol Denat., Fragrance, Sodium Citrate, Methylchloroisothiazolinone, Methylisothiazolinone, Benzophenone-4, Blue No. 1, Yellow No. 5

PACKAGE LABEL

LBLFR

LBLBK